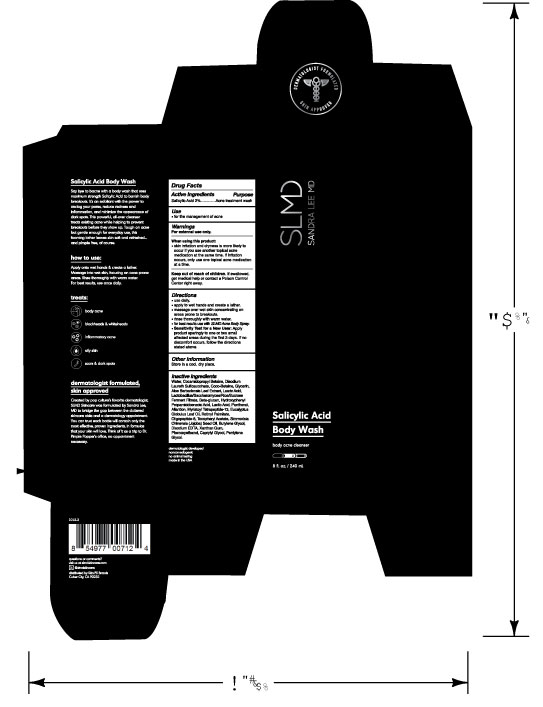 DRUG LABEL: SLMD Salicylic Acid Body Wash
NDC: 59958-405 | Form: LIQUID
Manufacturer: Owen Biosciences Inc.
Category: otc | Type: HUMAN OTC DRUG LABEL
Date: 20250113

ACTIVE INGREDIENTS: SALICYLIC ACID 2 g/100 g
INACTIVE INGREDIENTS: WATER 58.25 g/100 g; COCAMIDOPROPYL BETAINE 8.8 g/100 g; DISODIUM LAURETH SULFOSUCCINATE 8.5 g/100 g; GLYCERIN 5 g/100 g

Active Ingredients

Salicylic Acid 2%

Use

for the management of acne

Warnings For external use only

When using this product:
• skin irritation and dryness is more likely to
occur if you use another topical acne
medication at the same time. If irritation
occurs, only use one topical acne medication
at a time.

Keep out of reach of children.

If swallowed, get medical help or
contact a Poison Control Center
right away

Directions

• use daily.
• apply to wet hands and create a lather.
• massage over wet skin concentrating on
areas prone to breakouts.
• rinse thoroughly with warm water.
• for best results use with SLMD Acne Body Spray.
• Sensitivity Test for a New User: Apply
product sparingly to one or two small
affected areas during the first 3 days. If no
discomfort occurs, follow the directions
stated above.

Other information

Store in a cool, dry place.

Inactive Ingredients

Water, Cocamidopropyl Betaine, Disodium Laureth Sulfosuccinate, Coco-Betaine, Glycerin, Aloe Barbadensis Leaf Extract, Lauric Acid, Lactobacillus/Saccharomyces/Rice/Sucrose Ferment Filtrate, Beta-glucan, Hydroxyphenyl Propamidobenzoic Acid, Lactic Acid, Panthenol, Allantion, Myristoyl Tetrapeptide-13, Eucalyptus Globulus Leaf Oil, Retinyl Palmitate, Oligopeptide-8, Tocopheryl Acetate, Simmodsia Chinensis (Jojoba) Seed Oil, Butylene Glycol, Disodium EDTA, Xanthan Gum, Phenoxyethanol, Caprylyl Glycol, Pentylene Glycol.

Use

For the treatment of acne

SA Body Wash.jpg